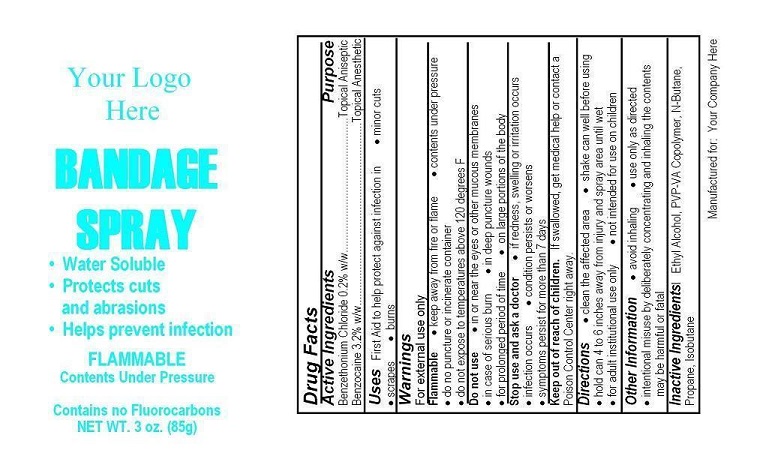 DRUG LABEL: Your Logo Here Bandage Aid
NDC: 52982-105 | Form: AEROSOL, SPRAY
Manufacturer: Dixon Investments, Inc.
Category: otc | Type: HUMAN OTC DRUG LABEL
Date: 20250128

ACTIVE INGREDIENTS: BENZOCAINE 2720 mg/85 g; BENZETHONIUM CHLORIDE 170 mg/85 g
INACTIVE INGREDIENTS: COPOVIDONE K25-31; ALCOHOL; BUTANE; PROPANE; ISOBUTANE

YOUR LOGO HERE BANDAGE SPRAY

Active Ingredients

Benzethonium Chloride 0.2% w/w
Benzocaine 3.2% w/w

Purpose

Topical Antiseptic
Topical Anesthetic

Uses

First Aid to help protect against infection in
minor cuts
scrapes
burns

Warnings

For external use only

Flammable
keep away from fire or flame
contents under pressure
do not puncture or incinerate container
do not expose to temperatures above 120°(F)

Do not use

in or near the eyes or other mucous membranes
in case of serious burn
in deep puncture wounds
for prolonged period of time
on large portions of the body

Stop use and ask a doctor

if redness, swelling, or irritation occurs
infection occurs
condition persists or worsens
symptoms persist for more than 7 days

Keep out of reach of children

If swallowed, get medical help or contact a Poison Control Center right away.

Directions

clean the affected area
shake can well before using
hold can 4 to 6 inches away from injury and spray area until wet
for adult institutional use only
not intended for use on children

Other information

avoid inhaling
use only as directed
intentional misuse by deliberately concentrating and inhaling the contents may be harmful or fatal

Inactive Ingredients

Ethyl Alcohol, PVP-VA Copolymer, N-Butane, Propane, Isobutane